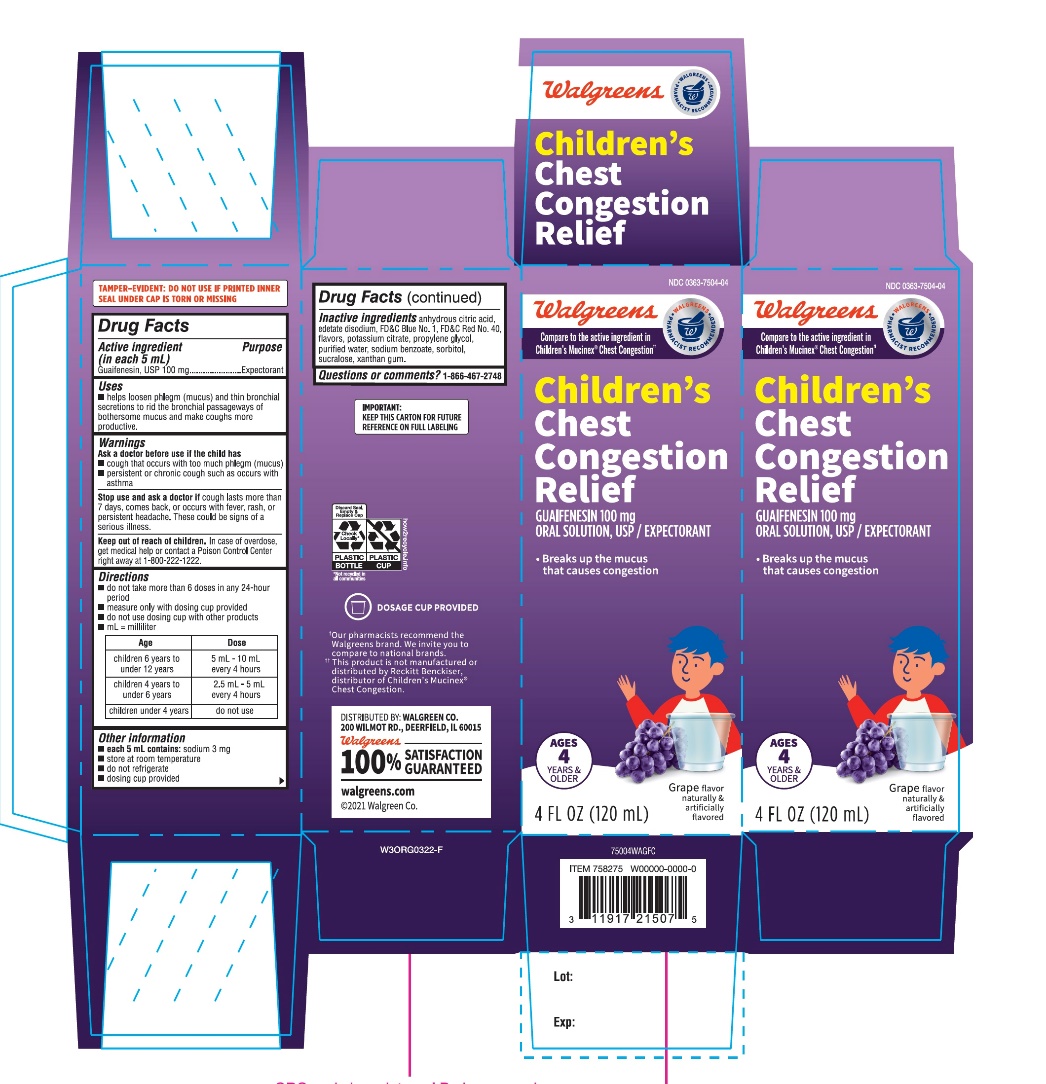 DRUG LABEL: Childrens Chest Congestion Relief
NDC: 0363-7504 | Form: SOLUTION
Manufacturer: WALGREENS COMPANY
Category: otc | Type: HUMAN OTC DRUG LABEL
Date: 20251126

ACTIVE INGREDIENTS: GUAIFENESIN 100 mg/5 mL
INACTIVE INGREDIENTS: ANHYDROUS CITRIC ACID; EDETATE DISODIUM; FD&C BLUE NO. 1; FD&C RED NO. 40; POTASSIUM CITRATE; PROPYLENE GLYCOL; WATER; SODIUM BENZOATE; SORBITOL; SUCRALOSE; XANTHAN GUM

Walgreen’s Children’s Chest Congestion Relief Grape Flavor 4 FL OZ (120 mL)

Drug Facts

Active ingredient (in each 5 mL)

Guaifenesin, USP 100 mg

Purpose

Expectorant

Uses

- helps loosen phlegm (mucus) and thin bronchial secretions to rid the bronchial passageways of bothersome mucus and make coughs more productive

Warnings

Ask a doctor before use if the child has

- cough that occurs with too much phlegm (mucus)
- persistent or chronic cough such as occurs with asthma

Stop use and ask a doctor ifcough lasts more than 7 days, comes back, or occurs with fever, rash, or persistent headache. These could be signs of a serious illness.

Keep out of reach of children.In case of overdose, get medical help or contact a Poison Control Center right away.

Directions

- do not take more than 6 doses in any 24-hour period
- measure only with dosing cup provided
- do not use dosing cup with other products
- mL = milliliter

Age | Dose
children 6 years to under 12 years | 5 mL – 10 mL every 4 hours
children 4 years to under 6 years | 2.5 mL – 5 mL every 4 hours
children under 4 years | do not use

Other information

- each 5 mL contains: sodium 3 mg
- store at room temperature
- do not refrigerate
- dosing cup provided

Inactive ingredients

anhydrous citric acid, edetate disodium, FD&C Blue No. 1, FD&C Red No. 40, natural and artificial flavors, potassium citrate propylene glycol, purified water, sodium benzoate, sorbitol, sucralose, xanthan gum.

Principal Display Panel - 120 mL

NDC 0363-7504-04

Compare to Children’s Mucinex®Chest Congestion active ingredient††

children's

Chest Congestion Relief

GUAIFENESIN 100 mg

ORAL SOLUTION, USP/

EXPECTORANT

ALCIHOL FREE

- Breaks up the mucus that causes congstion

AGES 4 YEARS & OLDERS

GRAPE FLAVOR

NATURALLY AND ARTIFICIALLY FLAVORED

4 FL OZ (120 mL)

IMPORTANT:Keep this carton for future reference on full labeling.

†Walgreens Pharmacist Survey

††This product is not manufactured or distributed by Reckitt Benckiser, distributor of Children’s Mucinex®Chest Congestion

DISTRIBUTED BY:

WALGREEN CO.

200 WILTMOT RD. DEERFIELD, IL 60015

Walgreens

100% SATISFACTION GUARANTEED

walgreen.com ©2020 Walgreens Co.